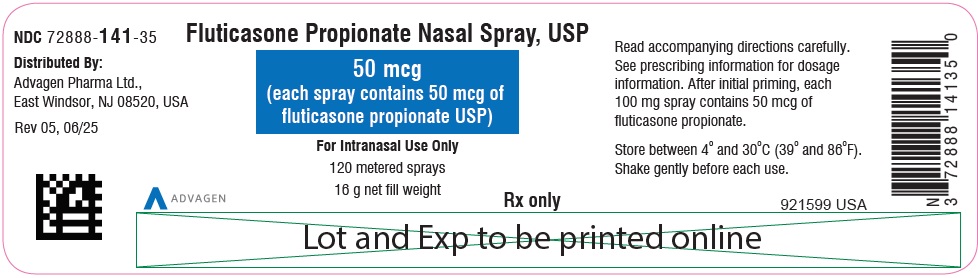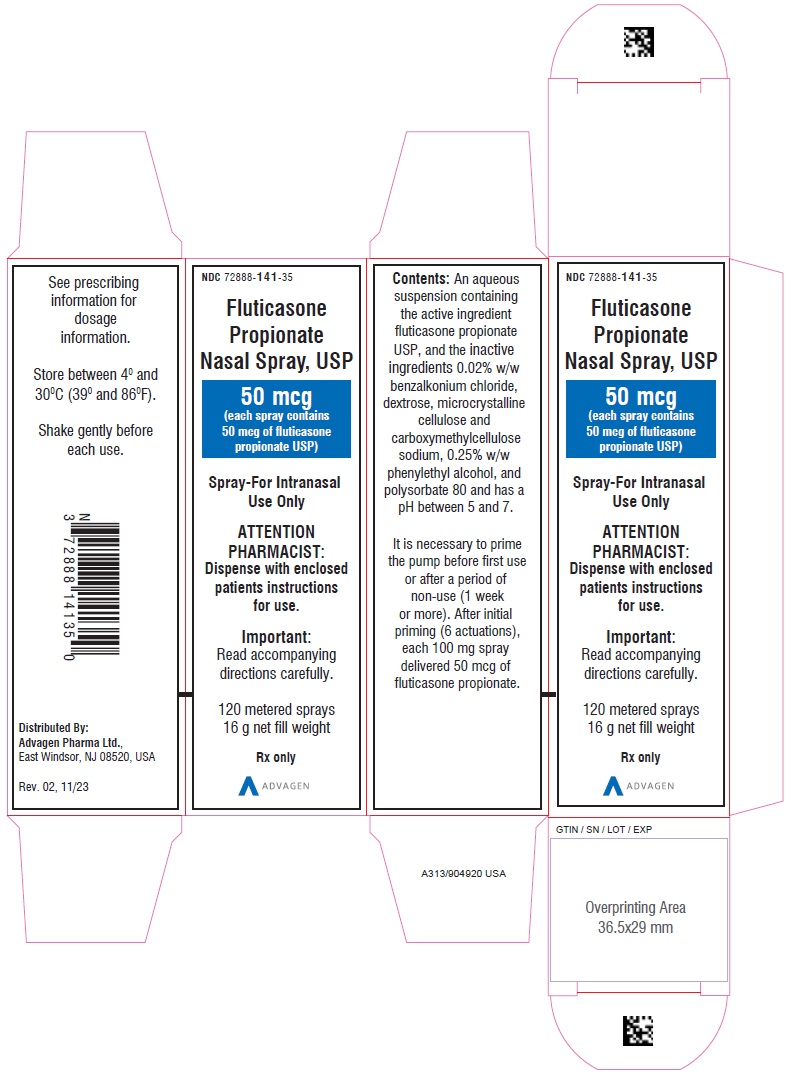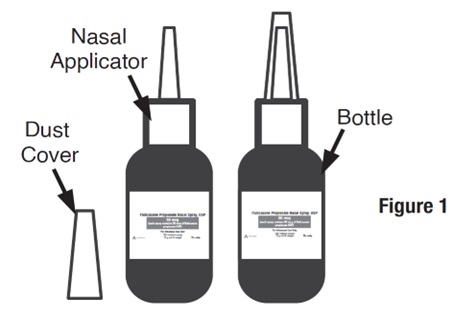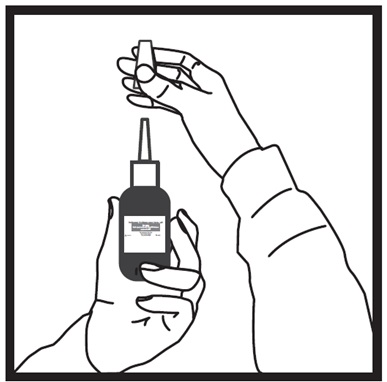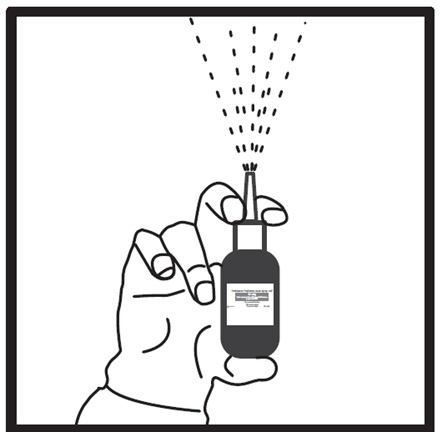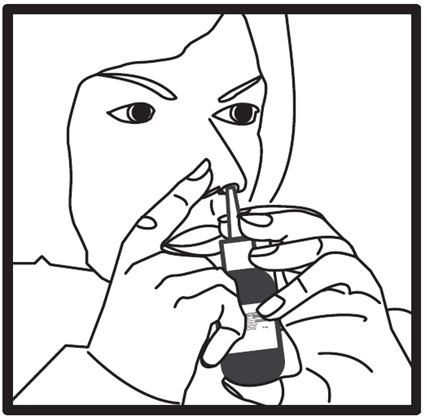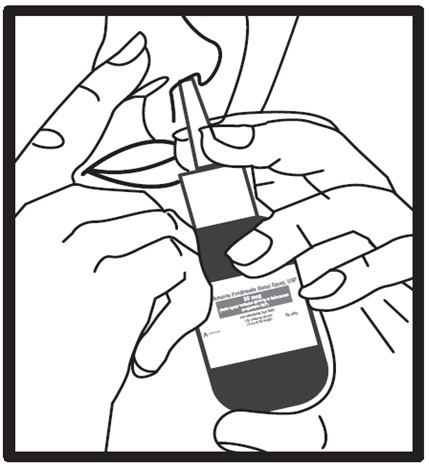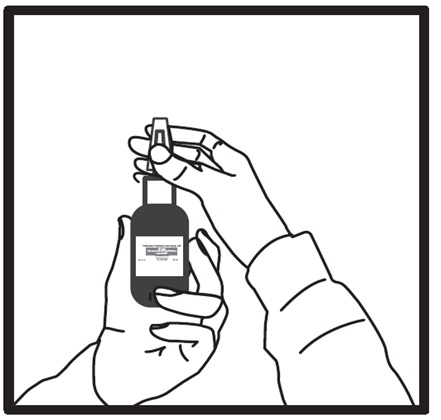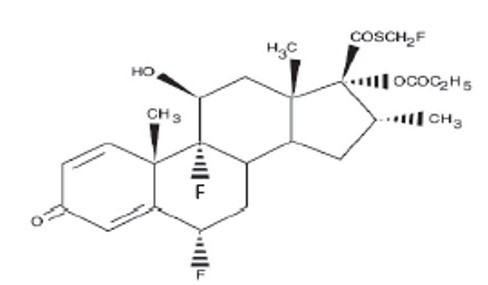 DRUG LABEL: FLUTICASONE PROPIONATE
NDC: 72888-141 | Form: SPRAY
Manufacturer: Advagen Pharma Ltd
Category: prescription | Type: HUMAN PRESCRIPTION DRUG LABEL
Date: 20260204

ACTIVE INGREDIENTS: FLUTICASONE PROPIONATE 50 ug/1 1
INACTIVE INGREDIENTS: BENZALKONIUM CHLORIDE; DEXTROSE; MICROCRYSTALLINE CELLULOSE; CARBOXYMETHYLCELLULOSE SODIUM; PHENYLETHYL ALCOHOL; POLYSORBATE 80

HIGHLIGHTS OF PRESCRIBING INFORMATION

These highlights do not include all the information needed to use FLUTICASONE
PROPIONATE NASAL SPRAY safely and effectively. See full prescribing information for FLUTICASONE PROPIONATE NASAL SPRAY.
FLUTICASONE PROPIONATE nasal spray
Initial U.S. Approval: 1994

RECENT MAJOR CHANGES

Warnings and Precautions, Glaucoma and Cataracts (5.2) 1/2019

1 INDICATIONS AND USAGE

Fluticasone propionate nasal spray is a corticosteroid indicated for the management of the nasal symptoms of perennial nonallergic rhinitis in adult and pediatric patients aged 4 years and older. (1)

2 DOSAGE AND ADMINISTRATION

For intranasal use only. Recommended starting dosages:
• Adults: 2 sprays per nostril once daily (200 mcg per day). (2.1)
• Adolescents and children aged 4 years and older: 1 spray per nostril once daily (100 mcg per day). (2.2)

3 DOSAGE FORMS AND STRENGTHS

Nasal spray: 50 mcg of fluticasone propionate USP in each 100 mg spray.

4 CONTRAINDICATIONS

Hypersensitivity to any ingredient.

5 WARNINGS AND PRECAUTIONS

- Epistaxis, nasal ulceration, Candida albicansinfection, nasal septal perforation, and impaired wound healing. Monitor patients periodically for signs of adverse effects on the nasal mucosa. Avoid use in patients with recent nasal ulcers, nasal surgery, or nasal trauma. (5.1)
- Glaucoma and cataracts: Consider referral to an ophthalmologist in patients who develop ocular symptoms or use fluticasone propionate nasal spray long-term. (5.2)
- Hypersensitivity reactions (e.g., anaphylaxis, angioedema, urticaria, contact dermatitis, and rash) have been reported after administration of fluticasone propionate nasal spray. Discontinue fluticasone propionate nasal spray if such reactions occur. (5.3)
- Potential worsening of infections (e.g., existing tuberculosis; fungal, bacterial, viral, or parasitic infection; ocular herpes simplex). Use with caution in patients with these infections. More serious or even fatal course of chickenpox or measles can occur in susceptible patients. (5.4)
- Hypercorticism and adrenal suppression may occur with very high dosages or at the regular dosage in susceptible individuals. If such changes occur, discontinue fluticasone propionate nasal spray slowly. (5.5)
- Monitor growth of pediatric patients. (5.7)

6 ADVERSE REACTIONS

The most common adverse reactions (>3%) are headache, pharyngitis, epistaxis, nasal burning/nasal irritation, nausea/vomiting, asthma symptoms, and cough. (6.1)

To report SUSPECTED ADVERSE REACTIONS, contact Advagen Pharma Ltd at 866-488-0312 or FDA at 1-800-FDA-1088 or www.fda.gov/medwatch.

7 DRUG INTERACTIONS

Strong cytochrome P450 3A4 inhibitors (e.g., ritonavir, ketoconazole): Use not recommended. May increase risk of systemic corticosteroid effects. (7.1)

8 USE IN SPECIFIC POPULATIONS

Hepatic impairment: Monitor patients for signs of increased drug exposure. (8.6)

FULL PRESCRIBING INFORMATION

1 INDICATIONS AND USAGE

Fluticasone propionate nasal spray is indicated for the management of the nasal symptoms of perennial nonallergic rhinitis in adults and pediatric patients aged 4 years and older.

2 DOSAGE AND ADMINISTRATION

Administer fluticasone propionate nasal spray by the intranasal route only. Prime fluticasone propionate nasal spray before using for the first time or after a period of non-use (1 week or more) by shaking the contents well and releasing 6 sprays into the air away from the face. Shake fluticasone propionate nasal spray gently before each use.

Patients should use fluticasone propionate nasal spray at regular intervals since its effectiveness depends on its regular use. Maximum effect may take several days and individual patients will experience a variable time to onset and different degree of symptom relief.

2.1 Adults

The recommended starting dosage in adults is 2 sprays (50 mcg of fluticasone propionate each) in each nostril once daily (total daily dose, 200 mcg). The same total daily dose, 1 spray in each nostril administered twice daily (e.g., 8 a.m. and 8 p.m.) is also effective. After the first few days, patients may be able to reduce their dose to 1 spray in each nostril once daily for maintenance therapy.

Maximum total daily doses should not exceed 2 sprays in each nostril (total dose, 200 mcg/day). There is no evidence that exceeding the recommended dose is more effective.

2.2 Adolescents and Children (Aged 4 Years and Older)

The recommended starting dosage in adolescents and children, aged 4 years and older is 1 spray in each nostril once daily (total daily dose, 100 mcg). Patients not adequately responding to 1 spray in each nostril may use 2 sprays in each nostril once daily (total daily dose, 200 mcg). Once adequate control is achieved, the dosage should be decreased to 1 spray in each nostril once daily.

The maximum total daily dosage should not exceed 2 sprays in each nostril (200 mcg/day). There is no evidence that exceeding the recommended dose is more effective.

3 DOSAGE FORMS AND STRENGTHS

Fluticasone propionate nasal spray USP is an aqueous suspension. Each 100-mg spray delivers 50 mcg of fluticasone propionate USP.

4 CONTRAINDICATIONS

Fluticasone propionate nasal spray is contraindicated in patients with hypersensitivity to any of its ingredients [see Warnings and Precautions (5.3), Description (11)] .

5 WARNINGS AND PRECAUTIONS

5.1 Local Nasal Effects

Epistaxis

In clinical trials of 2 to 26 weeks’ duration, epistaxis was observed more frequently in subjects treated with fluticasone propionate nasal spray than those who received placebo [See Adverse Reactions (6.1)] .

Nasal Ulceration

Postmarketing cases of nasal ulceration have been reported in patients treated with fluticasone propionate nasal spray [see Adverse Reactions (6.2)] .

CandidaInfection

In clinical trials with fluticasone propionate administered intranasally, the development of localized infections of the nose and pharynx with Candida albicans has occurred. When such an infection develops, it may require treatment with appropriate local therapy and discontinuation of fluticasone propionate nasal spray. Patients using fluticasone propionate nasal spray over several months or longer should be examined periodically for evidence of Candida infection or other signs of adverse effects on the nasal mucosa.

Nasal Septal Perforation

Postmarketing cases of nasal septal perforation have been reported in patients treated with fluticasone propionate nasal spray [see Adverse Reactions (6.2)] .

Impaired Wound Healing

Because of the inhibitory effect of corticosteroids on wound healing, patients who have experienced recent nasal ulcers, nasal surgery, or nasal trauma should avoid using fluticasone propionate nasal spray until healing has occurred.

5.2 Glaucoma and Cataracts

Use of intranasal and inhaled corticosteroids may result in the development of glaucoma and/or cataracts. Therefore, close monitoring is warranted in patients with a change in vision or with a history of increased intraocular pressure, glaucoma, and/or cataracts. Consider referral to an ophthalmologist in patients who develop ocular symptoms or use fluticasone propionate nasal spray long-term

5.3 Hypersensitivity Reactions including Anaphylaxis

Hypersensitivity reactions (e.g., anaphylaxis, angioedema, urticaria, contact dermatitis, and rash) have been reported after administration of fluticasone propionate nasal spray. Discontinue fluticasone propionate nasal spray if such reactions occur [see Contraindications (4)] . Rarely, immediate hypersensitivity reactions may occur after the administration of fluticasone propionate nasal spray.

5.4 Immunosuppression

Persons who are using drugs that suppress the immune system are more susceptible to infections than healthy individuals. Chickenpox and measles, for example, can have a more serious or even fatal course in susceptible children or adults using corticosteroids. In such children or adults who have not had these diseases or been properly immunized, particular care should be taken to avoid exposure. How the dose, route, and duration of corticosteroid administration affect the risk of developing a disseminated infection is not known. The contribution of the underlying disease and/or prior corticosteroid treatment to the risk is also not known. If a patient is exposed to chickenpox, prophylaxis with varicella zoster immune globulin (VZIG) may be indicated. If a patient is exposed to measles, prophylaxis with pooled intramuscular immunoglobulin (IG) may be indicated. (See the complete prescribing information for VZIG and IG.) If chickenpox develops, treatment with antiviral agents may be considered.

Intranasal corticosteroids should be used with caution, if at all, in patients with active or quiescent tuberculous infections of the respiratory tract; systemic fungal, bacterial, viral, or parasitic infections; or ocular herpes simplex.

5.5 Hypercorticism and Adrenal Suppression

When intranasal corticosteroids are used at higher than recommended dosages or in susceptible individuals at recommended dosages, systemic corticosteroid effects such as hypercorticism and adrenal suppression may appear. If such changes occur, the dosage of fluticasone propionate nasal spray should be discontinued slowly consistent with accepted procedures for discontinuing oral corticosteroid therapy.

The replacement of a systemic corticosteroid with a topical corticosteroid can be accompanied by signs of adrenal insufficiency. In addition, some patients may experience symptoms of corticosteroid withdrawal (e.g., joint and/or muscular pain, lassitude, depression). Patients previously treated for prolonged periods with systemic corticosteroids and transferred to topical corticosteroids should be carefully monitored for acute adrenal insufficiency in response to stress. In patients who have asthma or other clinical conditions requiring long-term systemic corticosteroid treatment, rapid decreases in systemic corticosteroid dosages may cause a severe exacerbation of their symptoms.

5.6 Drug Interactions with Strong Cytochrome P450 3A4 Inhibitors

The use of strong cytochrome P450 3A4 (CYP3A4) inhibitors (e.g., ritonavir, atazanavir, clarithromycin, indinavir, itraconazole, nefazodone, nelfinavir, saquinavir, ketoconazole, telithromycin, conivaptan, lopinavir, nefazodone, voriconazole) with fluticasone propionate nasal spray is not recommended because increased systemic corticosteroid adverse effects may occur [see Drug Interactions (7.1), Clinical Pharmacology (12.3)] .

5.7 Effect on Growth

Intranasal corticosteroids may cause a reduction in growth velocity when administered to pediatric patients [see Use in Specific Populations (8.4)] . Monitor the growth routinely of pediatric patients receiving fluticasone propionate nasal spray. To minimize the systemic effects of intranasal corticosteroids, including fluticasone propionate nasal spray, titrate each patient’s dose to the lowest dosage that effectively controls his/her symptoms [see Dosage and Administration (2), Use in Specific Populations (8.4)] .

6 ADVERSE REACTIONS

Systemic and local corticosteroid use may result in the following:

- Epistaxis, nasal ulceration, Candida albicans infection, nasal septal perforation, and impaired wound healing [see Warnings and Precautions (5.1)]
- Glaucoma and cataracts [see Warnings and Precautions (5.2)]
- Immunosuppression [see Warnings and Precautions (5.4)]
- Hypercorticism and adrenal suppression [see Warnings and Precautions (5.5)]
- Effect on growth [see Warnings and Precautions (5.7)]

6.1 Clinical Trials Experience

Because clinical trials are conducted under widely varying conditions, adverse reaction rates observed in the clinical trials of a drug cannot be directly compared with rates in the clinical trials of another drug and may not reflect the rates observed in practice.

In controlled US clinical trials, more than 3,300 subjects with allergic and nonallergic rhinitis received treatment with intranasal fluticasone propionate. In general, adverse reactions in clinical trials have been primarily associated with irritation of the nasal mucous membranes, and the adverse reactions were reported with approximately the same frequency by subjects treated with placebo. Less than 2% of subjects in clinical trials discontinued because of adverse reactions; this rate was similar for vehicle placebo and active comparators.

The safety data described below are based on 7 placebo-controlled clinical trials in subjects with allergic rhinitis. The 7 trials included 536 subjects (57 girls and 108 boys aged 4 to 11 years, 137 female and 234 male adolescents and adults) treated with fluticasone propionate nasal spray 200 mcg once daily over 2 to 4 weeks and 2 placebo-controlled clinical trials which included 246 subjects (119 female and 127 male adolescents and adults) treated with fluticasone propionate nasal spray 200 mcg once daily over 6 months (Table 1). Also included in Table 1 are adverse reactions from 2 trials in which 167 children (45 girls and 122 boys aged 4 to 11 years) were treated with fluticasone propionate nasal spray 100 mcg once daily for 2 to 4 weeks.

Table 1. Adverse Reactions with Fluticasone propionate Nasal Spray with >3% Incidence and More Common than Placebo in Subjects≥ 4 Years with Allergic Rhinitis

Adverse Reaction | Fluticasone propionate 100 mcg; Once Daily; (n = 167); % | Fluticasone propionate 200 mcg; Once Daily; (n = 782); % | Placebo; (n = 758); %
Headache | 6.6 | 16.1 | 14.6
Pharyngitis | 6 | 7.8 | 7.2
Epistaxis | 6 | 6.9 | 5.4
Nasal burning/nasal irritation | 2.4 | 3.2 | 2.6
Nausea/vomiting | 4.8 | 2.6 | 2
Asthma symptoms | 7.2 | 3.3 | 2.9
Cough | 3.6 | 3.8 | 2.8

Other adverse reactions with fluticasone propionate nasal spray observed with an incidence less than or equal to 3% but greater than or equal to 1% and more common than with placebo included: blood in nasal mucus, runny nose, abdominal pain, diarrhea, fever, flu-like symptoms, aches and pains, dizziness, and bronchitis.

6.2 Postmarketing Experience

In addition to adverse events reported from clinical trials, the following adverse events have been identified during post approval use of intranasal fluticasone propionate. Because these reactions are reported voluntarily from a population of uncertain size, it is not always possible to reliably estimate their frequency or establish a causal relationship to drug exposure. These events have been chosen for inclusion due to either their seriousness, frequency of reporting, or causal connection to fluticasone propionate or a combination of these factors.

General Disorders and Administration Site Conditions

Hypersensitivity reactions, including angioedema, skin rash, edema of the face and tongue, pruritus, urticaria, bronchospasm, wheezing, dyspnea, and anaphylaxis/anaphylactoid reactions, which in rare instances were severe.

Ear and Labyrinth Disorders

Alteration or loss of sense of taste and/or smell and, rarely, nasal septal perforation, nasal ulcer, sore throat, throat irritation and dryness, cough, hoarseness, and voice changes.

Eye Disorders

Dryness and irritation, conjunctivitis, blurred vision, glaucoma, increased intraocular pressure, and cataracts.

Cases of growth suppression have been reported for intranasal corticosteroids, including fluticasone propionate nasal spray [see Warnings and Precautions (5.7)] .

7 DRUG INTERACTIONS

7.1 Inhibitors of Cytochrome P450 3A4

Fluticasone propionate is a substrate of CYP3A4. The use of strong CYP3A4 inhibitors (e.g., ritonavir, atazanavir, clarithromycin, indinavir, itraconazole, nefazodone, nelfinavir, saquinavir, ketoconazole, telithromycin, conivaptan, lopinavir, nefazodone, voriconazole) with fluticasone propionate nasal spray is not recommended because increased systemic corticosteroid adverse effects may occur.

Ritonavir

A drug interaction trial with fluticasone propionate aqueous nasal spray in healthy subjects has shown that ritonavir (a strong CYP3A4 inhibitor) can significantly increase plasma fluticasone propionate exposure, resulting in significantly reduced serum cortisol concentrations [see Clinical Pharmacology (12.3)]. During postmarketing use, there have been reports of clinically significant drug interactions in patients receiving fluticasone propionate products, including fluticasone propionate nasal spray, with ritonavir, resulting in systemic corticosteroid effects including Cushing’s syndrome and adrenal suppression.

Ketoconazole

Coadministration of orally inhaled fluticasone propionate (1,000 mcg) and ketoconazole (200 mg once daily) resulted in a 1.9-fold increase in plasma fluticasone propionate exposure and a 45% decrease in plasma cortisol area under the curve (AUC), but had no effect on urinary excretion of cortisol.

8 USE IN SPECIFIC POPULATIONS

8.1 Pregnancy

Risk Summary

There are insufficient data on the use of fluticasone propionate nasal spray in pregnant women to inform a drug-associated risk. In animals, teratogenicity characteristic of corticosteroids, decreased fetal body weight and/or skeletal variations, were observed in rats, mice, and rabbits with subcutaneously administered maternal toxic doses of fluticasone propionate 5 times, equivalent to, and less than the maximum recommended human daily intranasal dose (MRHDID) on a mcg/m^2 basis, respectively. (See Animal Data.) However, fluticasone propionate administered via nose-only inhalation to rats decreased fetal body weight, but did not induce teratogenicity at a maternal toxic dose equivalent to the MRHDID on a mcg/m^2 basis. (See Animal Data.) Experience with oral corticosteroids suggests that rodents are more prone to teratogenic effects from corticosteroids than humans.

The estimated risk of major birth defects and miscarriage for the indicated population is unknown. All pregnancies have a background risk of birth defect, loss, or other adverse outcomes. In the U.S. general population, the estimated risk of major birth defects and miscarriage in clinically recognized pregnancies is 2% to 4% and 15% to 20%, respectively.

Data

Human Data: Following inhaled administration, fluticasone propionate was detected in the neonatal cord blood after delivery.

Animal Data: In embryofetal development studies with pregnant rats and mice dosed by the subcutaneous route throughout the period of organogenesis, fluticasone propionate was teratogenic in both species. Omphalocele, decreased body weight, and skeletal variations were observed in rat fetuses, in the presence of maternal toxicity, at a dose approximately 5 times the MRHDID of 200 mcg/day (on a mcg/m^2 basis with a maternal subcutaneous dose of 100 mcg/kg/day). The rat no observed adverse effect level (NOAEL) was observed at approximately equivalent to the MRHDID (on a mcg/m^2 basis with a maternal subcutaneous dose of 30 mcg/kg/day). Cleft palate and fetal skeletal variations were observed in mouse fetuses at a dose approximately equivalent to the MRHDID (on a mcg/m^2 basis with a maternal subcutaneous dose of 45 mcg/kg/day). The mouse NOAEL was observed with a dose approximately 0.3 times the MRHDID (on a mcg/m^2 basis with a maternal subcutaneous dose of 15 mcg/kg/day).

In an embryofetal development study with pregnant rats dosed by the nose-only inhalation route throughout the period of organogenesis, fluticasone propionate produced decreased fetal body weights and skeletal variations, in the presence of maternal toxicity, at a dose approximately equivalent to the MRHDID (on a mcg/m^2 basis with a maternal nose-only inhalation dose of 25.7 mcg/kg/day); however, there was no evidence of teratogenicity. The NOAEL was observed with a dose approximately 0.25 times the MRHDID (on a mcg/m^2 basis with a maternal nose-only inhalation dose of 5.5 mcg/kg/day).

In an embryofetal development study in pregnant rabbits that were dosed by the subcutaneous route throughout organogenesis, fluticasone propionate produced reductions of fetal body weights, in the presence of maternal toxicity, at doses approximately 0.06 times the MRHDID and higher (on a mcg/m^2 basis with a maternal subcutaneous dose of 0.57 mcg/kg/day). Teratogenicity was evident based upon a finding of cleft palate for 1 fetus at a dose 0.39 times the MRHDID (on a mcg/m^2 basis with a maternal subcutaneous dose of 4 mcg/kg/day). The NOAEL was observed in rabbit fetuses with a dose approximately 0.01 times the MRHDID (on a mcg/m^2 basis with a maternal subcutaneous dose of 0.08 mcg/kg/day).

Fluticasone propionate crossed the placenta following subcutaneous administration to mice and rats and oral administration to rabbits.

In a pre- and post-natal development study in pregnant rats dosed from late gestation through delivery and lactation (Gestation Day 17 to Postpartum Day 22), fluticasone propionate was not associated with decreases in pup body weight, and had no effects on developmental landmarks, learning, memory, reflexes, or fertility at doses up to 2 times the MRHDID (on a mcg/m^2 basis with maternal subcutaneous doses up to 50 mcg/kg/day).

8.2 Lactation

Risk Summary

There are no available data on the presence of fluticasone propionate in human milk, the effects on the breastfed child, or the effects on milk production. Low concentrations of other corticosteroids have been detected in human milk. The developmental and health benefits of breastfeeding should be considered along with the mother’s clinical need for fluticasone propionate nasal spray and any potential adverse effects on the breastfed child from fluticasone propionate nasal spray or from the underlying maternal condition.

Data

Animal Data:Subcutaneous administration of tritiated fluticasone propionate at a dose of 10 mcg/kg/day to lactating rats resulted in measurable levels in milk.

8.4 Pediatric Use

The safety and effectiveness of fluticasone propionate nasal spray in children aged 4 years and older have been established [ see Adverse Reactions (6.1), Clinical Pharmacology (12.3) ]. Six hundred fifty (650) subjects aged 4 to 11 years and 440 subjects aged 12 to 17 years were studied in US clinical trials with fluticasone propionate nasal spray. The safety and effectiveness of fluticasone propionate nasal spray in children younger than 4 years have not been established.

Effects on Growth

Controlled clinical trials have shown that intranasal corticosteroids may cause a reduction in growth velocity when administered to pediatric patients. This effect was observed in the absence of laboratory evidence of hypothalamic-pituitary-adrenal (HPA) axis suppression, suggesting that growth velocity is a more sensitive indicator of systemic corticosteroid exposure in pediatric patients than some commonly used tests of HPA axis function. The long-term effects of this reduction in growth velocity associated with intranasal corticosteroids, including the impact on final adult height, are unknown. The potential for “catch-up” growth following discontinuation of treatment with intranasal corticosteroids has not been adequately studied. The growth of pediatric patients receiving intranasal corticosteroids, including fluticasone propionate nasal spray, should be monitored routinely (e.g., via stadiometry). The potential growth effects of prolonged treatment should be weighed against the clinical benefits obtained and the risks associated with alternative therapies. To minimize the systemic effects of intranasal corticosteroids, including fluticasone propionate nasal spray, each patient’s dosage should be titrated to the lowest dosage that effectively controls his/her symptoms.

A 1-year placebo-controlled trial was conducted in 150 pediatric subjects (aged 3 to 9 years) to assess the effect of fluticasone propionate nasal spray (single daily dose of 200 mcg) on growth velocity. From the primary population receiving fluticasone propionate nasal spray (n=56) and placebo (n=52), the point estimate for growth velocity with fluticasone propionate nasal spray was 0.14 cm/year lower than placebo (95% CI:-0.54, 0.27 cm/year). Thus, no statistically significant effect on growth was noted compared with placebo. No evidence of clinically relevant changes in HPA axis function or bone mineral density was observed as assessed by 12-hour urinary cortisol excretion and dual-energy x-ray absorptiometry, respectively.

The potential for fluticasone propionate nasal spray to cause growth suppression in susceptible patients or when given at higher than recommended dosages cannot be ruled out.

8.5 Geriatric Use

A limited number of subjects aged 65 years and older (n=129) or 75 years and older (n=11) have been treated with fluticasone propionate nasal spray in clinical trials. While the number of subjects is too small to permit separate analysis of efficacy and safety, the adverse reactions reported in this population were similar to those reported by younger patients. In general, dose selection for an elderly patient should be cautious, usually starting at the low end of the dosing range, reflecting the greater frequency of decreased hepatic, renal, or cardiac function, and of concomitant disease or other drug therapy.

8.6 Hepatic Impairment

Formal pharmacokinetic trials using fluticasone propionate nasal spray have not been conducted in subjects with hepatic impairment. Since fluticasone propionate is predominantly cleared by hepatic metabolism, impairment of liver function may lead to accumulation of fluticasone propionate in plasma. Therefore, patients with hepatic disease should be closely monitored.

8.7 Renal Impairment

Formal pharmacokinetic trials using fluticasone propionate nasal spray have not been conducted in subjects with renal impairment.

10 OVERDOSAGE

Chronic overdosage may result in signs/symptoms of hypercorticism [see Warnings and Precautions (5.5)]. Intranasal administration of 2 mg (10 times the recommended dose) of fluticasone propionate twice daily for 7 days was administered to healthy human volunteers. Adverse events reported with fluticasone propionate were similar to placebo, and no clinically significant abnormalities in laboratory safety tests were observed. Single oral doses up to 16 mg have been studied in human volunteers with no acute toxic effects reported. Repeat oral doses up to 80 mg daily for 10 days in volunteers and repeat oral doses up to 10 mg daily for 14 days in patients were well tolerated. Adverse reactions were of mild or moderate severity, and incidences were similar in active and placebo treatment groups. Acute overdosage with this dosage form is unlikely since one bottle of fluticasone propionate nasal spray contains approximately 8 mg of fluticasone propionate.

11 DESCRIPTION

The active component of fluticasone propionate nasal spray USP is fluticasone propionate USP, a corticosteroid having the chemical name S-(fluoromethyl)6α,9-difluoro-11β-17-dihydroxy-16α-methyl-3-oxoandrosta-1,4-diene-17β-carbothioate, 17-propionate and the following chemical structure:

Fluticasone propionate is a white to off-white powder with a molecular weight of 500.6 and the molecular formula is C25H31F3O5S. It is practically insoluble in water, freely soluble in dimethyl sulfoxide and dimethylformamide, and slightly soluble in methanol and 95% ethanol.
Fluticasone propionate nasal spray, 50 mcg is an aqueous suspension of microfine fluticasone propionate for topical administration to the nasal mucosa by means of a metering, atomizing spray pump. Fluticasone propionate nasal spray also contains 0.02% w/w benzalkonium chloride, dextrose, microcrystalline cellulose and carboxymethylcellulose sodium, 0.25% w/w phenylethyl alcohol and polysorbate 80 and has a pH between 5 and 7.

After initial priming, each actuation delivers 50 mcg of fluticasone propionate in 100 mg of formulation through the nasal adapter.

12 CLINICAL PHARMACOLOGY

12.1 Mechanism of Action

Fluticasone propionate is a synthetic, trifluorinated corticosteroid with anti-inflammatory activity. Fluticasone propionate has been shown in vitro to exhibit a binding affinity for the human glucocorticoid receptor that is 18 times that of dexamethasone, almost twice that of beclomethasone-17-monopropionate (BMP), the active metabolite of beclomethasone dipropionate, and over 3 times that of budesonide. Data from the McKenzie vasoconstrictor assay in man are consistent with these results. The clinical significance of these findings is unknown.

The precise mechanism through which fluticasone propionate affects rhinitis symptoms is not known. Corticosteroids have been shown to have a wide range of effects on multiple cell types (e.g., mast cells, eosinophils, neutrophils, macrophages, lymphocytes) and mediators (e.g., histamine, eicosanoids, leukotrienes, cytokines) involved in inflammation. In 7 trials in adults, fluticasone propionate nasal spray has decreased nasal mucosal eosinophils in 66% of patients (35% for placebo) and basophils in 39% of patients (28% for placebo). The direct relationship of these findings to long-term symptom relief is not known.

12.2 Pharmacodynamics

HPA Axis Effect

The potential systemic effects of fluticasone propionate nasal spray on the HPA axis were evaluated. Fluticasone propionate nasal spray given as 200 mcg once daily or 400 mcg twice daily was compared with placebo or oral prednisone 7.5 or 15 mg given in the morning. Fluticasone propionate nasal spray at either dosage for 4 weeks did not affect the adrenal response to 6-hour cosyntropin stimulation, while both dosages of oral prednisone significantly reduced the response to cosyntropin.

Cardiac Electrophysiology

A study specifically designed to evaluate the effect of fluticasone propionate nasal spray on the QT interval has not been conducted.

12.3 Pharmacokinetics

The activity of fluticasone propionate nasal spray is due to the parent drug, fluticasone propionate. Due to the low bioavailability by the intranasal route, the majority of the pharmacokinetic data was obtained via other routes of administration.

Absorption

Indirect calculations indicate that fluticasone propionate delivered by the intranasal route has an absolute bioavailability averaging less than 2%. Trials using oral dosing of labeled and unlabeled drug have demonstrated that the oral systemic bioavailability of fluticasone propionate is negligible (<1%), primarily due to incomplete absorption and presystemic metabolism in the gut and liver. After intranasal treatment of patients with rhinitis for 3 weeks, fluticasone propionate plasma concentrations were above the level of detection (50 pg/mL) only when recommended doses were exceeded and then only in occasional samples at low plasma levels.

Distribution

Following intravenous administration, the initial disposition phase for fluticasone propionate was rapid and consistent with its high lipid solubility and tissue binding. The volume of distribution averaged 4.2 L/kg.

The percentage of fluticasone propionate bound to human plasma proteins averaged 99%. Fluticasone propionate is weakly and reversibly bound to erythrocytes and is not significantly bound to human transcortin.

Elimination

Following intravenous dosing, fluticasone propionate showed polyexponential kinetics and had a terminal elimination half-life of approximately 7.8 hours. The total blood clearance of fluticasone propionate is high (average: 1,093 mL/min), with renal clearance accounting for less than 0.02% of the total.

Metabolism:The only circulating metabolite detected in man is the 17β-carboxylic acid derivative of fluticasone propionate, which is formed through the CYP3A4 pathway. This metabolite had less affinity (approximately 1/2,000) than the parent drug for the glucocorticoid receptor of human lung cytosol in vitroand negligible pharmacological activity in animal studies. Other metabolites detected in vitrousing cultured human hepatoma cells have not been detected in man.

Excretion:Less than 5% of a radiolabeled oral dose was excreted in the urine as metabolites, with the remainder excreted in the feces as parent drug and metabolites.

Special Populations

Fluticasone propionate nasal spray was not studied in any special populations, and no gender-specific pharmacokinetic data have been obtained.

Drug Interactions

Inhibitors of Cytochrome P450 3A4: Ritonavir:Fluticasone propionate is a substrate of CYP3A4. Coadministration of fluticasone propionate and the strong CYP3A4 inhibitor, ritonavir, is not recommended based upon a multiple-dose, crossover drug interaction trial in 18 healthy subjects. Fluticasone propionate aqueous nasal spray (200 mcg once daily) was coadministered for 7 days with ritonavir (100 mg twice daily). Plasma fluticasone propionate concentrations following fluticasone propionate aqueous nasal spray alone were undetectable (<10 pg/mL) in most subjects, and when concentrations were detectable, peak levels (Cmax) averaged 11.9 pg/mL (range: 10.8 to 14.1 pg/mL) and AUC(0-τ)averaged 8.43 pg•h/mL (range: 4.2 to 18.8 pg•h/mL). Fluticasone propionate Cmaxand AUC(0-τincreased to 318 pg/mL (range: 110 to 648 pg/mL) and 3,102.6 pg•h/mL (range: 1,207.1 to 5,662.0 pg•h/mL), respectively, after coadministration of ritonavir with fluticasone propionate aqueous nasal spray. This significant increase in plasma fluticasone propionate exposure resulted in a significant decrease (86%) in serum cortisol AUC.

Ketoconazole:Coadministration of orally inhaled fluticasone propionate (1,000 mcg) and ketoconazole (200 mg once daily) resulted in a 1.9-fold increase in plasma fluticasone propionate exposure and a 45% decrease in plasma cortisol AUC, but had no effect on urinary excretion of cortisol.

Erythromycin:In a multiple-dose drug interaction study, coadministration of orally inhaled fluticasone propionate (500 mcg twice daily) and erythromycin (333 mg 3 times daily) did not affect fluticasone propionate pharmacokinetics.

13 NONCLINICAL TOXICOLOGY

13.1 Carcinogenesis, Mutagenesis, Impairment of Fertility

Fluticasone propionate demonstrated no tumorigenic potential in mice at oral doses up to 1,000 mcg/kg (approximately 25 and 20 times the MRHDID in adults and children, respectively, on a mcg/m^2 basis) for 78 weeks or in rats at inhalation doses up to 57 mcg/kg (approximately 3 and 2 times the MRHDID in adults and children, respectively, on a mcg/m^2 basis) for 104 weeks.

Fluticasone propionate did not induce gene mutation in prokaryotic or eukaryotic cells in vitro. No significant clastogenic effect was seen in cultured human peripheral lymphocytes in vitro or in the mouse micronucleus test.

Fertility and reproductive performance were unaffected in male and female rats at subcutaneous doses up to 50 mcg/kg (approximately 2 times the MRHDID in adults on a mcg/m^2 basis).

14 CLINICAL STUDIES

Perennial Nonallergic Rhinitis

Three randomized, double-blind, parallel-group, vehicle placebo-controlled trials were conducted in 1,191 subjects to investigate regular use of fluticasone propionate nasal spray in subjects with perennial nonallergic rhinitis. These trials evaluated subject-rated total nasal symptom scores (TNSS) that included nasal obstruction, postnasal drip, rhinorrhea in subjects treated for 28 days of double-blind therapy and in 1 of the 3 trials for 6 months of open-label treatment. Two of these trials demonstrated that subjects treated with fluticasone propionate nasal spray (100 mcg twice daily) exhibited statistically significant decreases in TNSS compared with subjects treated with vehicle.

16 HOW SUPPLIED/STORAGE AND HANDLING

Fluticasone Propionate Nasal Spray USP, 50 mcg is supplied in an amber glass bottle fitted with a white metering atomizing pump, white nasal adapter fitted with a clear plastic dust cap, in a box of one (NDC 72888-141-35) with FDA-approved Patient Labeling (see Patient Instructions for Use for proper actuation of the device). Each bottle contains a net fill weight of 16 g and will provide 120 actuations. Each actuation delivers 50 mcg of fluticasone propionate in 100 mg of formulation through the nasal adapter. The correct amount of medication in each spray cannot be assured after 120 sprays even though the bottle is not completely empty. The bottle should be discarded when the labeled number of actuations has been used.

Store between 4° and 30°C (39° and 86°F).

17 PATIENT COUNSELING INFORMATION

Advise the patient to read the FDA-approved patient labeling (Patient Information and Instructions for Use).

Local Nasal Effects

Inform patients that treatment with fluticasone propionate nasal spray may lead to adverse reactions, which include epistaxis and nasal ulceration. Candida infection may also occur with treatment with fluticasone propionate nasal spray. In addition, fluticasone propionate nasal spray has been associated with nasal septal perforation and impaired wound healing. Patients who have experienced recent nasal ulcers, nasal surgery, or nasal trauma should not use fluticasone propionate nasal spray until healing has occurred [see Warnings and Precautions (5.1)] .

Glaucoma and Cataracts

Inform patients that glaucoma and cataracts are associated with nasal and inhaled corticosteroid use. Advise patients to notify their healthcare providers if a change in vision is noted while using fluticasone propionate nasal spray [see Warnings and Precautions (5.2)] .

Hypersensitivity Reactions, including Anaphylaxis

Inform patients that hypersensitivity reactions, including anaphylaxis, angioedema, urticaria, contact dermatitis, and rash, may occur after administration of fluticasone propionate nasal spray. If such reactions occur, patients should discontinue use of fluticasone propionate nasal spray [see Warnings and Precautions (5.3)].

Immunosuppression

Warn patients who are on immunosuppressant doses of corticosteroids to avoid exposure to chickenpox or measles and if they are exposed to consult their healthcare provider without delay. Inform patients of potential worsening of existing tuberculosis; fungal, bacterial, viral, or parasitic infections; or ocular herpes simplex [see Warnings and Precautions (5.4)] .

Reduced Growth Velocity

Advise parents that fluticasone propionate nasal spray may cause a reduction in growth velocity when administered to pediatric patients. Physicians should closely follow the growth of children and adolescents taking corticosteroids by any route [see Warnings and Precautions (5.7), Pediatric Use (8.4)] .

Use Daily for Best Effect

Inform patients that they should use fluticasone propionate nasal spray on a regular basis. Fluticasone propionate nasal spray, like other corticosteroids, does not have an immediate effect on rhinitis symptoms. Maximum benefit may not be reached for several days. Patients should not increase the prescribed dosage but should contact their healthcare providers if symptoms do not improve or if the condition worsens.

Keep Spray Out of Eyes and Mouth

Inform patients to avoid spraying fluticasone propionate nasal spray in their eyes and mouth.

Distributed by:
Advagen Pharma Ltd.,
East Windsor, NJ 08520, USA

Rev. 06/2025

Patient Information
Fluticasone Propionate (floo tik’ a sone proe’ pee oh nate)
Nasal Spray USP, 50 mcg

What isfluticasone propionatenasal spray?

Fluticasone propionate nasal spray is a prescription medicine used to treat non-allergy nasal symptoms such as runny nose, stuffy nose, sneezing, and nasal itching in adults and children aged 4 years and older.

It is not known if fluticasone propionate nasal spray is safe and effective in children younger than 4 years of age.

Do not usefluticasone propionatenasal sprayif you are allergic to fluticasone propionate or any of the ingredients in fluticasone propionate nasal spray. See “What are the ingredients in fluticasone propionate nasal spray?” below for a complete list of ingredients.

Before usingfluticasone propionatenasal spray, tell your healthcare provider about all of your medical conditions, including if you:

- have or have had nasal sores, nasal surgery, or nasal injury.
- have or have had eye problems, such as glaucoma or cataracts.
- have an immune system problem.
- have any type of viral, bacterial, or fungal infection.
- are exposed to chickenpox or measles.
- are pregnant or planning to become pregnant. It is not known if fluticasone propionate nasal spray may harm your unborn baby.
- are breastfeeding or plan to breastfeed. It is not known if fluticasone passes into your breast milk and if it can harm your baby.

Tell your healthcare provider about all the medicines you take,including prescription and over-the-counter medicines, vitamins, and herbal supplements. Fluticasone propionate nasal spray and certain other medicines may interact with each other. This may cause serious side effects.

Especially, tell your healthcare provider if you take antifungal or anti-HIV medicines.

Know the medicines you take. Keep a list of them to show your healthcare provider and pharmacist when you get a new medicine.

How should I usefluticasone propionatenasal spray?

- Read the step-by-step instructions for usingfluticasone propionatenasal spray at the end of this Patient Information.
- Fluticasone propionate nasal spray is for use in your nose only. Do not spray it in your eyes or mouth.
- Children should use fluticasone propionate nasal spray with an adult’s help, as instructed by the child’s healthcare provider.
- Use fluticasone propionate nasal spray exactly as your healthcare provider tells you. Do not use fluticasone propionate nasal spray more often than prescribed.
- Fluticasone propionate nasal spray may take several days of regular use for your rhinitis symptoms to get better. If your symptoms do not improve or get worse, call your healthcare provider.
- You will get the best results if you keep using fluticasone propionate nasal spray regularly each day without missing a dose. After you begin to feel better, your healthcare provider may decrease your dose. Do notstop using fluticasone propionate nasal spray unless your healthcare provider tells you to do so.

What are the possible side effects offluticasone propionatenasal spray?

Fluticasone propionatenasal spray may cause serious side effects, including:

- nose problems.Nose problems may include:
  - nose bleeds.
  - sores (ulcers) in your nose.
  - a certain fungal infection in your nose, mouth, or throat (thrush).
  - hole in the cartilage of your nose (nasal septal perforation).

Symptoms of nasal septal perforation may include:

-
  - crusting in the nose
  - nose bleeds
  - runny nose
  - whistling sound when you breathe
  - slow wound healing.You should not use fluticasone propionate nasal spray until your nose has healed if you have a sore in your nose, have had surgery on your nose, or if your nose has been injured.
- glaucoma and cataracts. Using nasal and inhaled corticosteroid medicines may result in you developing glaucoma and/or cataracts. Your healthcare provider may have you see an eye doctor (ophthalmologist) if you develop eye symptoms or use fluticasone propionate nasal spray for long periods of time. Tell your healthcare provider if you have any changes in your eye sight while using fluticasone propionate nasal spray.
- serious allergic reactions. Call your healthcare provider or get emergency medical care if you get any of the following signs of a serious allergic reaction:
  - rash
  - hives
  - swelling of your face, mouth, and tongue
  - breathing problems
- weakened immune system and increased chance of getting infections (immunosuppression). Taking medicines that weaken your immune system makes you more likely to get infections and can make certain infections worse. These infections may include tuberculosis (TB), ocular herpes simplex infections, and infections caused by fungi, bacteria, viruses, and parasites. Avoid contact with people who have a contagious disease such as chickenpox or measles while using fluticasone propionate nasal spray. If you come in contact with someone who has chickenpox or measles call your healthcare provider right away. Symptoms of an infection may include:
  - fever
  - feeling
  - tired
  - pain
  - nausea
  - aches
  - vomiting
  - chills
- lowered steroid hormone levels (adrenal insufficiency).Adrenal insufficiency happens when your adrenal glands do not make enough steroid hormones. This can happen when you stop taking oral corticosteroid medicines (such as prednisone) and start taking medicine containing an inhaled steroid (such as fluticasone propionate nasal spray). Symptoms of adrenal insufficiency may include:
  - feeling tired
  - lack of energy
  - weakness
  - nausea and vomiting
  - low blood pressure
- slowed growth in children. A child’s growth should be checked often.
  The most common side effects of fluticasone propionate nasal spray include:
- headache
- nausea and vomiting
- sore throat
- trouble breathing
- nose bleeds
- cough
- nose burning or itching

These are not all the possible side effects with fluticasone propionate nasal spray.

Call your doctor for medical advice about side effects. You may report side effects to FDA at

1-800-FDA-1088.

How do I store Fluticasone Propionate Nasal Spray?

- Store fluticasone propionate nasal spray between 39° and 86°F (4° and 30°C).

Keepfluticasone propionate nasal spray and all medicines out of the reach of children.

General information about the safe and effective use offluticasone propionate nasal spray.

Medicines are sometimes prescribed for purposes not mentioned in a Patient Information leaflet. Do not use fluticasone propionate nasal spray for a condition for which it was not prescribed. Do not give your fluticasone propionate nasal spray to other people, even if they have the same condition that you have. It may harm them.

You can ask your pharmacist or healthcare provider for information about fluticasone propionate nasal spray that was written for healthcare professionals.

What are the ingredients influticasone propionate nasal spray USP?

Active ingredient:fluticasone propionate USP.

Inactive ingredients:0.02% w/w benzalkonium chloride, dextrose, microcrystalline cellulose and carboxymethylcellulose sodium, 0.25% w/w phenylethyl alcohol and polysorbate 80.

For more information about fluticasone propionate nasal spray, call 866-488-0312.

Distributed by:
Advagen Pharma Limited,
East Windsor, NJ 08520, USA
Rev 11/2024

Instruction for Use

Fluticasone Propionate (flootik’ a sone proe’ pee oh nate)
Nasal Spray USP, 50 mcg

Fluticasone propionatenasal spray is for use in your nose only.

Read this information before you start using yourfluticasone propionatenasal spray.

Parts of your Fluticasone Propionate Nasal Spray USP, 50 mcg(See Figure 1)

Figure 1

Yourfluticasone propionatenasal spray must be primed before you use it for the first time and when you have not used it for a week or more.

How to prime yourfluticasone propionatenasal spray:

- Shake the bottle gently and then remove the dust cap (Figure 2).

Figure 2

- Hold the bottle as shown (Figure 3) with the nasal applicator pointing away from you and with your forefinger and middle finger on either side of the nasal applicator and your thumb underneath the bottle.
- Press down and release 6times until a fine spray appears (Figure 3). The pump is now ready for use.

Figure 3

Using your fluticasone propionate nasal spray:

Step 1:Blow your nose to clear your nostrils.

Step 2:Close 1nostril. Tilt your head forward slightly and, keeping the bottle upright, carefully insert the nasal applicator into the other nostril (Figure 4).

Figure 4

Step 3:Start to breathe in through your nose, and while breathing in press firmly and quickly down 1time on the applicator to release the spray. To get a full dose, use your forefinger and middle finger to spray while supporting the base of the bottle with your thumb. Avoid spraying in eyes. Breathe in gently through the nostril (Figure 5).

Figure 5

Step 4:Breathe out through your mouth.

Step 5:If a second spray is required in that nostril, repeat steps 2through 4.

Step 6:Repeat steps 2through 5in the other nostril.

Step 7:Wipe the nasal applicator with a clean tissue and replace the dust cap (Figure 6).

Figure 6

Do not use this bottle for more than the labeled number of sprays even though the bottle is not completely empty. Before you throw the bottle away, you should talk to your healthcare provider to see if a refill is needed. Do not take extra doses or stop taking fluticasone propionate nasal spray without talking to your healthcare provider.

Cleaning your fluticasone propionate nasal spray:

Your nasal spray should be cleaned at least 1time each week.

1. Remove the dust cap and then gently pull upwards to free the nasal applicator.
2. Wash the applicator and dust cap under warm tap water. Allow to dry at room temperature.
3. Place the applicator and dust cap back on the bottle.
4. If the nasal applicator becomes blocked, it can be removed and left to soak in warm water. Rinse the nasal applicator with cold tap water. Dry the nasal applicator and place it back on the bottle. Do not try to unblock the nasal applicator by inserting a pin or other sharp object.

Storing your fluticasone propionate nasal spray:

- Store fluticasone propionate nasal spray between 39° and 86°F (4° and 30°C).
- Do not use your fluticasone propionate nasal spray after the date shown as “EXP” on the label or box.

All trademarks are the property of their respective owners.

This Patient Information and Instructions for Use has been approved by the U.S. Food and Drug Administration.

Distributed by:
Advagen Pharma Ltd.,
East Windsor, NJ 08520, USA.
Rev. 11/2024

PACKAGE LABEL PRINCIPAL DISPLAY PANEL

Fluticasone Propionate Nasal Spray USP - 50 mcg 120 Metered Sprays- NDC 72888-141-35 - Bottle's Label

Fluticasone Propionate Nasal Spray USP - 50 mcg 120 Metered Sprays- NDC 72888-141-35 - Carton's Label